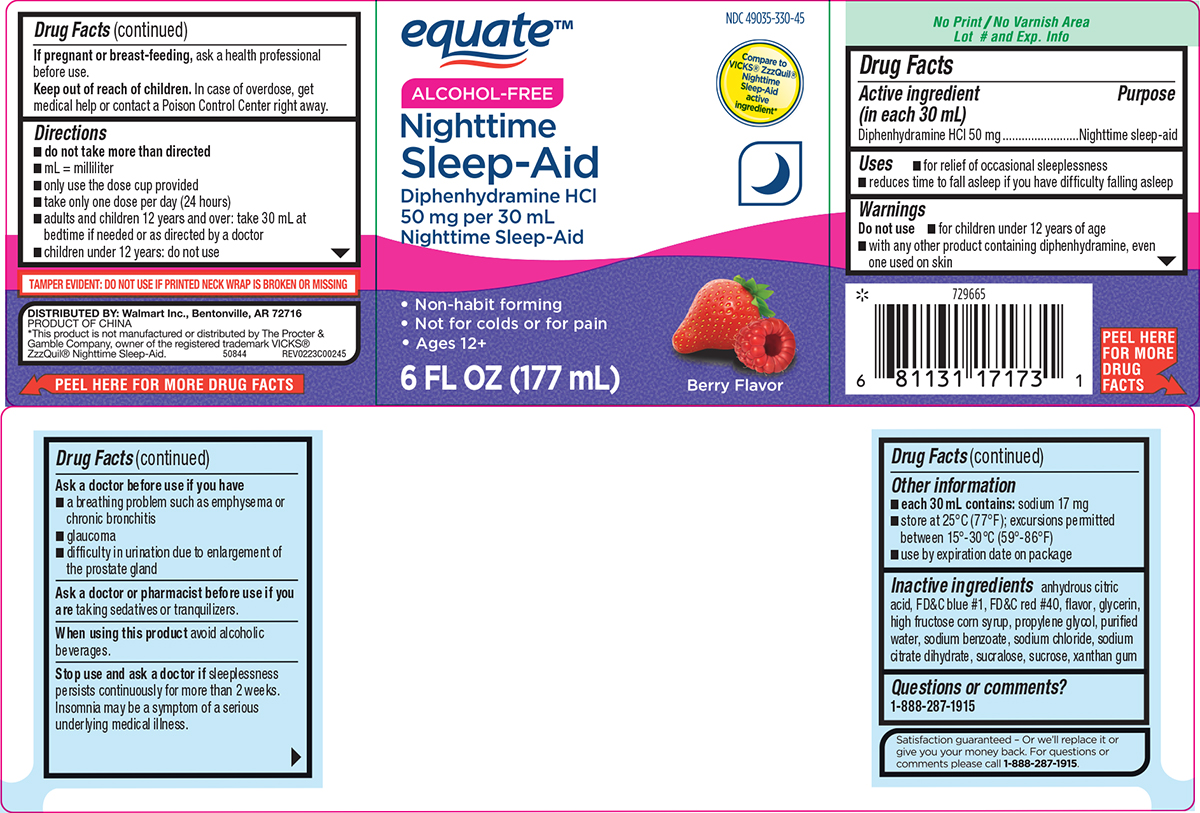 DRUG LABEL: Nighttime Sleep Aid
NDC: 49035-330 | Form: SOLUTION
Manufacturer: Wal-Mart Stores Inc
Category: otc | Type: HUMAN OTC DRUG LABEL
Date: 20260206

ACTIVE INGREDIENTS: DIPHENHYDRAMINE HYDROCHLORIDE 50 mg/30 mL
INACTIVE INGREDIENTS: ANHYDROUS CITRIC ACID; FD&C BLUE NO. 1; FD&C RED NO. 40; GLYCERIN; HIGH FRUCTOSE CORN SYRUP; PROPYLENE GLYCOL; WATER; SODIUM BENZOATE; SODIUM CHLORIDE; TRISODIUM CITRATE DIHYDRATE; SUCRALOSE; SUCROSE; XANTHAN GUM

Equate 44-002

Active ingredient (in each 30 mL)

Diphenhydramine HCl 50 mg

Purpose

Nighttime sleep-aid

Uses

- for relief of occasional sleeplessness
- reduces time to fall asleep if you have difficulty falling asleep

Warnings

Do not use

- for children under 12 years of age
- with any other product containing diphenhydramine, even one used on skin

Ask a doctor before use if you have

- a breathing problem such as emphysema or chronic bronchitis
- glaucoma
- difficulty in urination due to enlargement of the prostate gland

Ask a doctor or pharmacist before use if you are

taking sedatives or tranquilizers.

When using this product

avoid alcoholic beverages.

Stop use and ask a doctor if

sleeplessness persists continuously for more than 2 weeks. Insomnia may be a symptom of a serious underlying medical illness.

If pregnant or breast-feeding,

ask a health professional before use.

Keep out of reach of children.

In case of overdose, get medical help or contact a Poison Control Center right away.

Directions

- do not take more than directed
- mL = milliliter
- only use the dose cup provided
- take only one dose per day (24 hours)
- adults and children 12 years and over: take 30 mL at bedtime if needed or as directed by a doctor
- children under 12 years: do not use

Other information

- each 30 mL contains: sodium 17 mg
- store at 25°C (77°F); excursions permitted between 15°-30°C (59°-86°F)
- use by expiration date on package

Inactive ingredients

anhydrous citric acid, FD&C blue #1, FD&C red #40, flavor, glycerin, high fructose corn syrup, propylene glycol, purified water, sodium benzoate, sodium chloride, sodium citrate dihydrate, sucralose, sucrose, xanthan gum

Questions or comments?

1-888-287-1915

Principal Display Panel

equate™

NDC 49035-330-45

Compare to
VICKS® ZzzQuil®
Nighttime
Sleep-Aid
active
ingredient*

Nighttime
Sleep-Aid

Diphenhydramine HCl
50 mg per 30 mL
Nighttime Sleep-Aid

•Non-habit forming
•Not for colds or for pain
• Ages 12+

6 FL OZ (177 mL)

Berry Flavor

TAMPER EVIDENT: DO NOT USE IF PRINTED NECK WRAP IS BROKEN OR MISSING

DISTRIBUTED BY: Walmart Inc., Bentonville, AR 72716
PRODUCT OF CHINA
*This product is not manufactured or distributed by The Procter &
Gamble Company, owner of the registered trademark VICKS®
ZzzQuil® Nighttime Sleep-Aid. 50844 REV0223C00245

Equate 44-002A